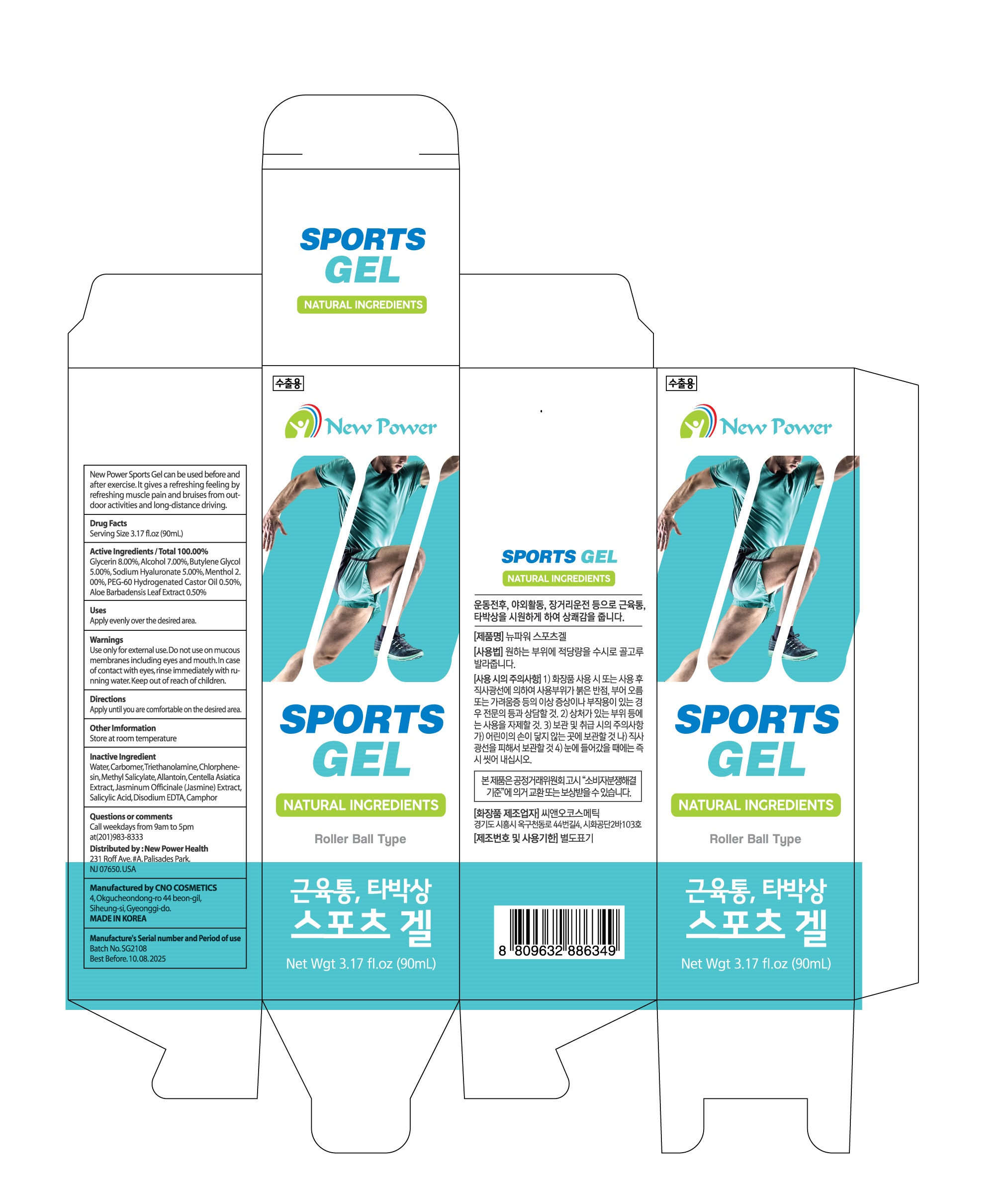 DRUG LABEL: SPORTS gel
NDC: 82145-0002 | Form: LIQUID
Manufacturer: Aloe Vera Korea Co.,Ltd.
Category: otc | Type: HUMAN OTC DRUG LABEL
Date: 20210803

ACTIVE INGREDIENTS: MENTHOL 2.5 g/100 mL
INACTIVE INGREDIENTS: WATER

Drug Facts

ACTIVE INGREDIENT

menthol

INACTIVE INGREDIENT

water, glycerin, etc

PURPOSE

before and after exercise, relax, naturally derived ingredients, fast absorption, minimize skin irritation

keep out of reach of the children

INDICATIONS AND USAGE

apply evenly over the desired area with bruise, muscle pain

WARNINGS

don’t use on the part where there is injury, eczema, or dermatitis

if swallowed, get medical help or contact a person control center immediately

DOSAGE AND ADMINISTRATION

for topical use only